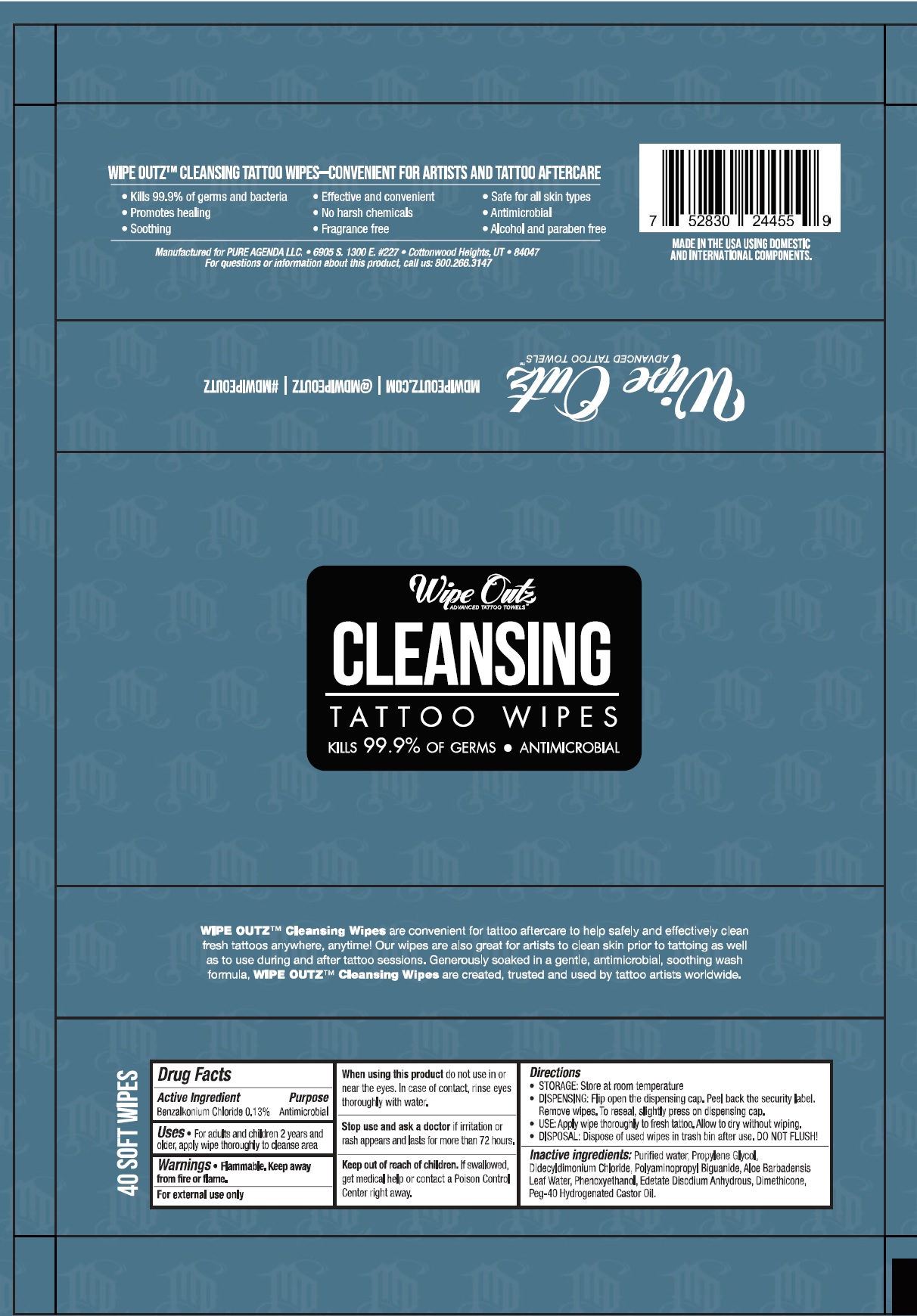 DRUG LABEL: Wipe Outz Cleansing Tattoo Wipes
NDC: 75266-003 | Form: CLOTH
Manufacturer: Purocol LLC
Category: otc | Type: HUMAN OTC DRUG LABEL
Date: 20220301

ACTIVE INGREDIENTS: BENZALKONIUM CHLORIDE 1.3 mg/1 mL
INACTIVE INGREDIENTS: WATER; PROPYLENE GLYCOL; DIDECYLDIMONIUM CHLORIDE; POLYAMINOPROPYL BIGUANIDE; ALOE VERA LEAF; PHENOXYETHANOL; EDETATE DISODIUM ANHYDROUS; DIMETHICONE; POLYOXYL 40 HYDROGENATED CASTOR OIL

Wipe Outz Cleansing Tattoo Wipes

Active Ingredient

Benzalkonium Chloride 0.13%

Purpose

Antimicrobial

Uses

- For adults and children 2 years and older, apply wipe thoroughly to cleanse area

Warnings

- Flammable. Keep away from fire or flame.
- For external use only.

When using this product

do not use in or near the eyes. In case of contact, rinse eyes thoroughly with water.

Stop use and ask a doctor if

irritation or rash appears and lasts for more than 72 hours.

Keep out of reach of children.

If swallowed, get medical help or contact Poison Control Center right away.

Directions

- STORAGE: Store at room temperature
- DISPENSING: Flip open the dispensing cap. Peel back the security label. Remove wipes. To reseal, slightly press on dispensing cap.
- USE: Apply wipe thoroughly to fresh tattoo. Allow to dry without wiping.
- DIPOSAL: Dispose of used wipes in trash bin after use. DO NOT FLUSH!

Inactive ingredients:

Purified water, Propylene Glycol, Didecyldimonium Chloride, Polyaminopropyl Biguanide, Aloe Barbadensis Lea Water, Phenoxyethanol, Edetate Disodium Anhydrous, Dimethicone, Peg-40 Hydrogenated Castor Oil.